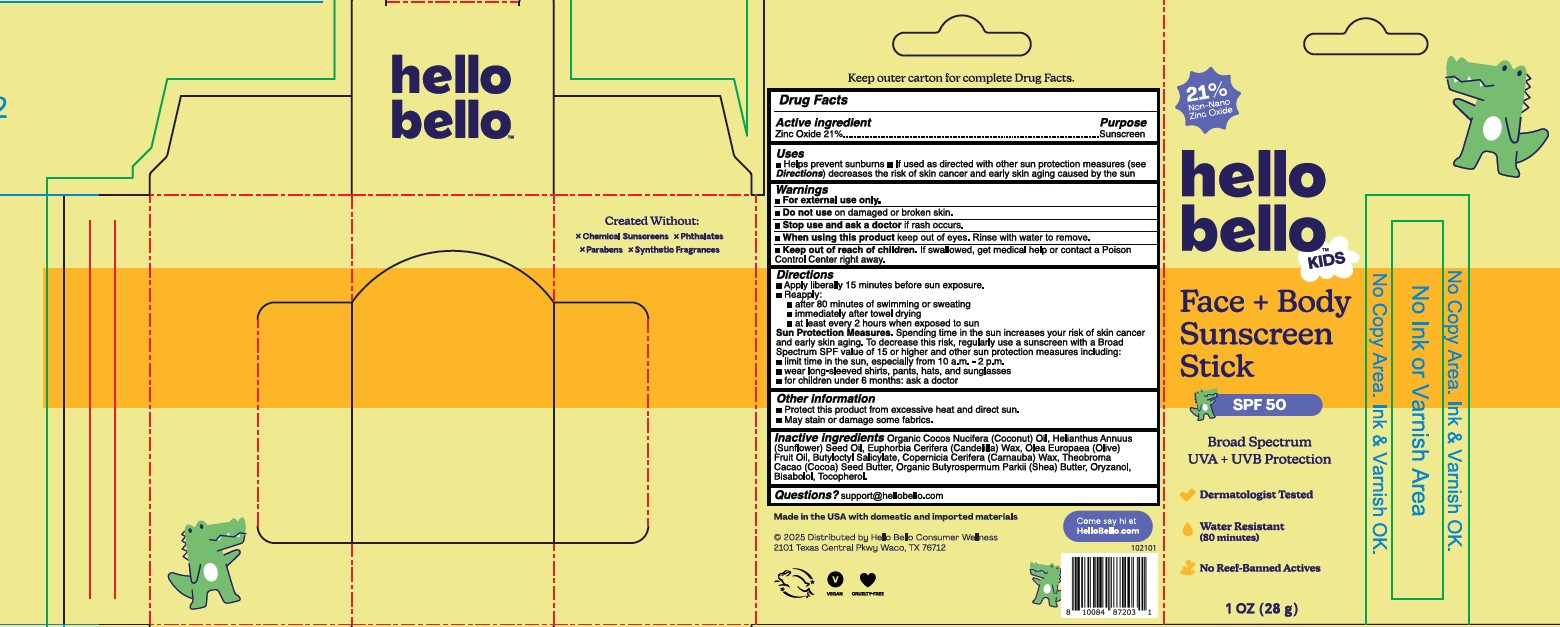 DRUG LABEL: Hello Bello Kids SPF 50 Face and Body Sunscreen Stick
NDC: 73418-115 | Form: STICK
Manufacturer: Hello Bello
Category: otc | Type: HUMAN OTC DRUG LABEL
Date: 20251016

ACTIVE INGREDIENTS: ZINC OXIDE 210 mg/1 g
INACTIVE INGREDIENTS: BISABOLOL; OLIVE OIL; COCOA BUTTER; SHEA BUTTER; CANDELILLA WAX; BUTYLOCTYL SALICYLATE; TOCOPHEROL; COCONUT OIL; ORYZANOL; CARNAUBA WAX; SUNFLOWER OIL

Hello Bello Kids SPF 50 Face & Body Sunscreen Stick

Active Ingredients

Zinc Oxide 21.0%

Purpose

Sunscreen

Uses

- Helps prevent sunburn
- If used as directed with other sun protection measures (see Directions), decreases the risk of skin cancer and early skin aging caused by the sun

Warnings

For external use only

Do not use on

broken or damaged skin

When using this product

Keep out of eyes. Rinse with water to remove

Stop use and ask a doctor if

rash occurs

Keep out of reach of children.

If swallowed, get medical help or contact a Poison Control Center right away

Directions

Apply liberally and spread evenly by hand 15 minutes before sun exposure
Reapply:
• after 80 minutes of swimming or sweating
• immediately after towel use
• at least every 2 hours
For children under 6 months of age, ask a doctor
Sun Protection Measures:Spending time in the sun can increase your risk of skin cancer and early skin aging. To decrease this risk, regularly use sunscreen with a Broad Spectrum SPF value of 15 or higher and other sun protection measures including: • Limit time in the sun, especially from 10a.m. - 2p.m. • Wear long-sleeved shirts, pants, hats and sunglasses

Other Information

- Protect the product in this container from excessive heat and direct sun
- Avoid long-term exposure storage above 40°C (104°F)
- May stain some fabrics

Inactive Ingredients

Bisabolol, Butyloctyl Salicylate, Butyrospermum Parkii (Shea) Butter*, Cocos Nucifera (Coconut) Oil*, Copernicia Cerifera (Carnauba) Wax, Euphorbia Cerifera (Candelila) Wax, Helianthus Annuus (Sunflower) Seed Oil, Olea Europaea (Olive) Fruit Oil, Oryzanol, Theobroma Cacao (Cocoa) Seed Butter, Tocopherol.
*Organic